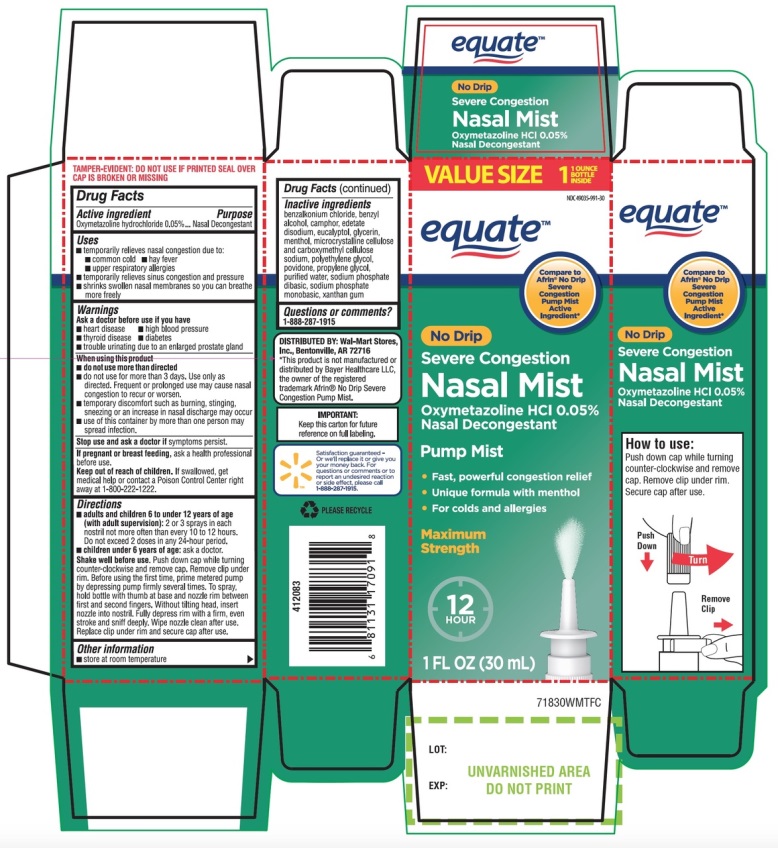 DRUG LABEL: No Drip Nasal Mist Nasal Decongestant Severe Congestion
NDC: 49035-991 | Form: SPRAY
Manufacturer: Wal-Mart Stores,Inc.,
Category: otc | Type: HUMAN OTC DRUG LABEL
Date: 20251027

ACTIVE INGREDIENTS: OXYMETAZOLINE HYDROCHLORIDE 0.05 g/100 mL
INACTIVE INGREDIENTS: BENZALKONIUM CHLORIDE; BENZYL ALCOHOL; CAMPHOR, (-)-; EDETATE DISODIUM; EUCALYPTOL; GLYCERIN; MENTHOL, UNSPECIFIED FORM; MICROCRYSTALLINE CELLULOSE; CARBOXYMETHYLCELLULOSE SODIUM, UNSPECIFIED; POLYETHYLENE GLYCOL 400; POVIDONE K90; PROPYLENE GLYCOL; WATER; SODIUM PHOSPHATE, DIBASIC, ANHYDROUS; SODIUM PHOSPHATE, MONOBASIC, ANHYDROUS; XANTHAN GUM

No Drip Nasal Mist Nasal Decongestant Severe Congestion 1 FL OZ 30mL

Active ingredient

Oxymetazoline hydrochloride 0.05%

Purpose

Nasal Decongestant

Uses

- temporarily relieves nasal congestion due to:
- common cold
- hay fever
- upper respiratory allergies
- temporarily relieves sinus congestion and pressure
- shrinks swollen nasal membranes so you can breathe more freely

Warnings

Ask a doctor before use if you have

- heart disease
- high blood pressure
- thyroid disease
- diabetes
- trouble urinating due to an enlarged prostate gland

When using this product

- do not use more than directed
- do not use for more than 3 days. Use only as directed. Frequent or prolonged use may cause nasal congestion to recur or worsen.
- temporary discomfort such as burning, stinging, sneezing or an increase in nasal discharge may occur
- use of this container by more than one person may spread infection

Stop use and ask a doctor if

symptoms persist.

If pregnant or breast-feeding,

ask a health professional before use.

Keep out of reach of children.

If swallowed, get medical help or contact a Poison Control Center right away at 1-800-222-1222.

Directions

- adults and children 6 to under 12 years of age (with adult supervision):2 or 3 sprays in each nostril not more often than every 10 to 12 hours. Do not exceed 2 doses in any 24-hour period.
- children under 6 years of age:ask a doctor

Shake well before use. Push down cap while turning counter-clockwise and remove cap. Remove clip under rim. Before using the first time, prime metered pump by depressing pump firmly several times. To spray, hold bottle with thumb at base and nozzle rim between first and second fingers. Without tilting head, insert nozzle into nostril. Fully depress rim with a firm, even stroke and sniff deeply. Wipe nozzle clean after use. Replace clip under rim and secure cap after use.

Other information

- store at room temperature

Inactive ingredients

benzalkonium chloride, benzyl alcohol, camphor, edetate disodium, eucalyptol, glycerin, menthol, microcrystalline cellulose and carboxymethyl cellulose sodium, polyethylene glycol, povidone, propylene glycol, purified water, sodium phosphate dibasic, sodium phosphate monobasic, xanthan gum.

Questions or comments?

1-888-287-1915

Principal Display Panel

NDC 49035-991-30

Compare to the active ingredient in Afrin®No-Drip Severe Congestion Pump Mist*

NO DRIP

NASAL MIST

Nasal Decongestant

Oxymetazoline HCl 0.05%

SEVERE CONGESTION

12 Hour Pump Mist

Fast, Powerful Congestion Relief

For Colds & Allergies

Maximum Strength

Unique Formula with Menthol

1 FL OZ (30 mL)

*This product is not manufactured and distributed by Bayer Healthcare LLC, distributor of Afrin®No Drip Severe Congestion Pump Mist.

IMPORTANT: Keep this carton for future reference on full labeling.

Satisfaction guaranteed or we’ll replace it or give you your money back. For questions or comments or to report an undesired reaction or side effect, please call 1-888-287-1915.

TAMPER EVIDENT: DO NOT USE IF SEAL OVER CAP IS BROKEN OR MISSING

DISTRIBUTED BY: Wal-Mart Stores, Inc.,

Bentonville, AR 72716